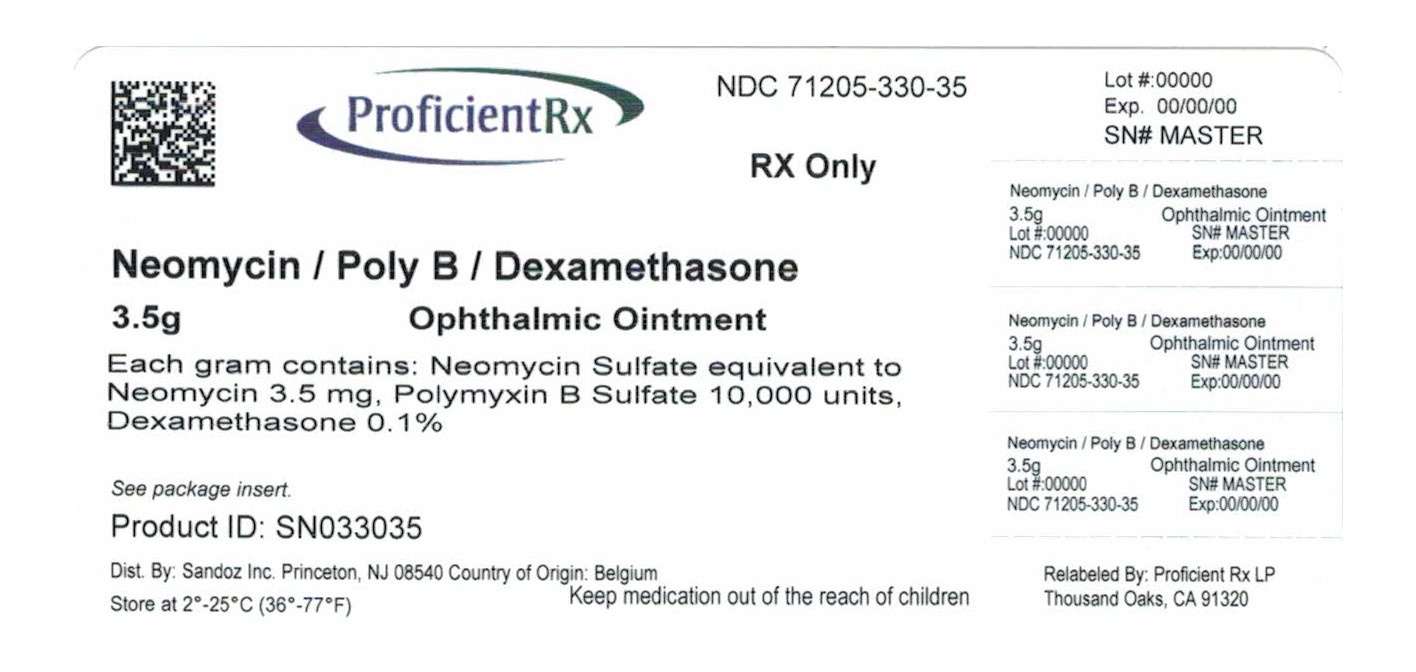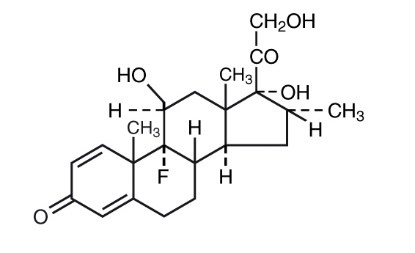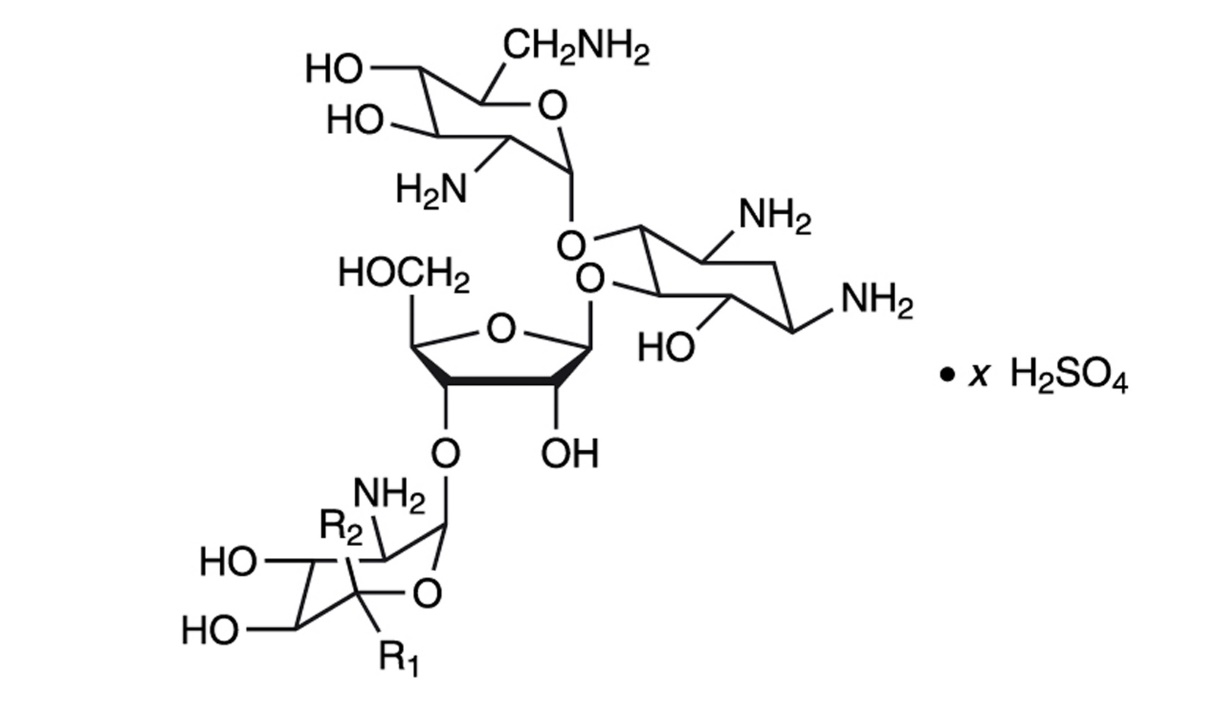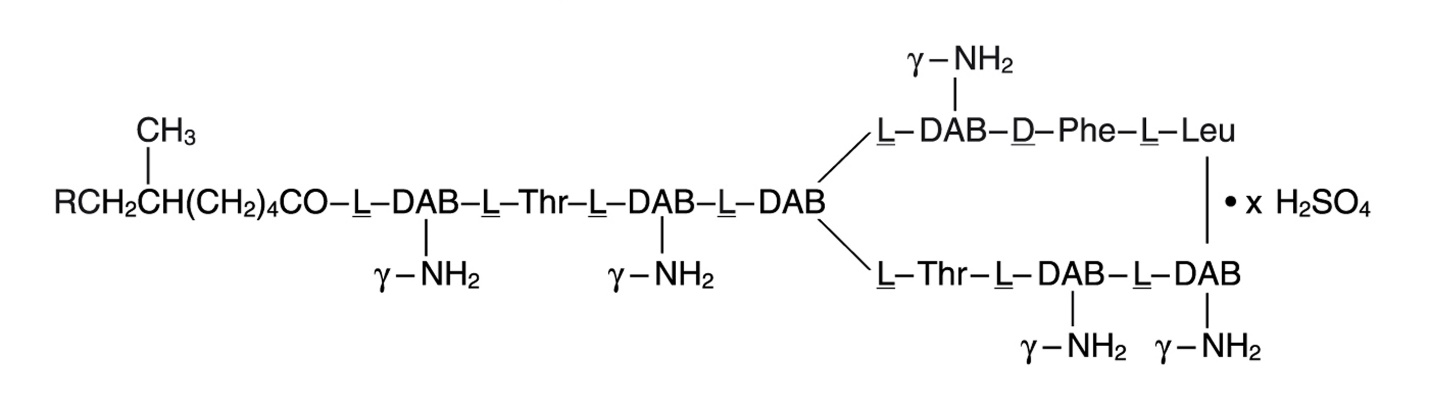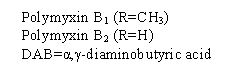 DRUG LABEL: Neomycin and Polymyxin B Sulfates and Dexamethasone
NDC: 71205-330 | Form: OINTMENT
Manufacturer: Proficient Rx LP
Category: prescription | Type: HUMAN PRESCRIPTION DRUG LABEL
Date: 20210101

ACTIVE INGREDIENTS: NEOMYCIN SULFATE 3.5 mg/1 g; POLYMYXIN B SULFATE 10000 [iU]/1 g; DEXAMETHASONE 1 mg/1 g
INACTIVE INGREDIENTS: METHYLPARABEN; PROPYLPARABEN; PETROLATUM; LANOLIN

Neomycin and Polymyxin B Sulfates and Dexamethasone Ophthalmic Ointment

DESCRIPTION

Neomycin and Polymyxin B Sulfates and Dexamethasone Ophthalmic Ointment is a multiple dose anti-infective steroid combination in sterile ointment form for topical application.

The chemical structure for the active ingredient Neomycin Sulfate is:

Neomycin B (R1=H, R2=CH2NH2)

Neomycin C (R1=CH2NH2, R2=H)

The chemical structure for the active ingredient Polymyxin B Sulfate is:

The chemical structure for the active ingredient Dexamethasone is:

C22H29FO5

MW = 392.47

Established Name:

Dexamethasone

Chemical Name:

Pregna-1, 4-diene-3, 20-dione, 9-fluoro-11,17, 21-trihydroxy-16-methyl-, (11β, 16α)-.

Each gram contains: Actives: neomycin sulfate equivalent to neomycin 3.5 mg, polymyxin B sulfate 10,000 units, dexamethasone 0.1%. Preservatives: methylparaben 0.05%, propylparaben 0.01%. Inactives: white petrolatum, anhydrous liquid lanolin.

CLINICAL PHARMACOLOGY

Corticoids suppress the inflammatory response to a variety of agents and they probably delay or slow healing. Since corticoids may inhibit the body's defense mechanism against infection, a concomitant antimicrobial drug may be used when this inhibition is considered to be clinically significant in a particular case.

When a decision to administer both a corticoid and an antimicrobial is made, the administration of such drugs in combination has the advantage of greater patient compliance and convenience, with the added assurance that the appropriate dosage of both drugs is administered, plus assured compatibility of ingredients when both types of drugs are in the same formulation and, particularly, that the correct volume of drug is delivered and retained.

The relative potency of corticosteroids depends on the molecular structure, concentration and release from the vehicle.

INDICATIONS AND USAGE

For steroid-responsive inflammatory ocular conditions for which a corticosteroid is indicated and where bacterial infection or a risk of bacterial ocular infection exists.

Ocular steroids are indicated in inflammatory conditions of the palpebral and bulbar conjunctiva, cornea, and anterior segment of the globe where the inherent risk of steroid use in certain infective conjunctivitides is accepted to obtain a diminution in edema and inflammation. They are also indicated in chronic anterior uveitis and corneal injury from chemical, radiation or thermal burns ; or penetration of foreign bodies.

The use of a combination drug with an anti-infective component is indicated where the risk of infection is high or where there is an expectation that potentially dangerous numbers of bacteria will be present in the eye.

The particular anti-infective drug in this product is active against the following common bacterial eye pathogens: Staphylococcus aureus, Escherichia coli, Haemophilus influenzae, Klebsiella/Enterobacter species, Neisseria species, and Pseudomonas aeruginosa.

This product does not provide adequate coverage against: Serratia marcescens and Streptococci, including Streptococcus pneumoniae.

CONTRAINDICATIONS

Epithelial herpes simplex keratitis (dendritic keratitis), vaccinia, varicella, and many other viral diseases of the cornea and conjunctiva. Mycobacterial infection of the eye. Fungal diseases of ocular structures. Hypersensitivity to a component of the medication. (Hypersensitivity to the antibiotic component occurs at a higher rate than for other components.)

WARNINGS

NOT FOR INJECTION. Do not touch tube tip to any surface, as this may contaminate the contents. Prolonged use may result in glaucoma, with damage to the optic nerve, defects in visual acuity and fields of vision, and posterior subcapsular cataract formation. Prolonged use may suppress the host response and thus increase the hazard of secondary ocular infections. In those diseases causing thinning of the cornea or sclera, perforations have been known to occur with the use of topical steroids. In acute purulent conditions of the eye, steroids may mask infection or enhance existing infection. If this product is used for 10 days or longer, intraocular pressure should be routinely monitored even though it may be difficult in children and uncooperative patients.

Products containing neomycin sulfate may cause cutaneous sensitization.

Employment of steroid medication in the treatment of herpes simplex requires great caution.

PRECAUTIONS

The initial prescription and renewal of the medication order beyond 8 g should be made by a physician only after examination of the patient with the aid of magnification, such as a slit lamp biomicroscopy and, where appropriate, fluorescein staining.

The possibility of persistent fungal infections of the cornea should be considered after prolonged steroid dosing.

Patients should be advised not to wear contact lenses if they have signs and symptoms of bacterial ocular infection.

Do not use the product if the imprinted carton seals have been damaged, or removed.

Pregnancy

Pregnancy Category C. Dexamethasone has been shown to be teratogenic in mice and rabbits following topical ophthalmic application in multiples of the therapeutic dose.

In the mouse, corticosteroids produce fetal resorptions and a specific abnormality, cleft palate. In the rabbit, corticosteroids have produced fetal resorptions and multiple abnormalities involving the head, ears, limbs, palate, etc.

There are no adequate or well-controlled studies in pregnant women. Neomycin and Polymyxin B Sulfates and Dexamethasone Ophthalmic Ointment should be used during pregnancy only if the potential benefit to the mother justifies the potential risk to the embryo or fetus. Infants born of mothers who have received substantial doses of corticosteroids during pregnancy should be observed carefully for signs of hypoadrenalism.

Nursing Mothers

Systemically administered corticosteroids appear in human milk and could suppress growth, interfere with endogenous corticosteroid production, or cause other untoward effects. It is not known whether topical administration of corticosteroids could result in sufficient systemic absorption to produce detectable quantities in human milk. Because many drugs are excreted in human milk, caution should be exercised when Neomycin and Polymyxin B Sulfates and Dexamethasone Ophthalmic Ointment is administered to a nursing woman.

Pediatrics

Safety and effectiveness in pediatric patients have not been established.

Geriatrics

No overall clinical differences in safety or effectiveness have been observed between the elderly and other adult patients.

ADVERSE REACTIONS

Adverse reactions have occurred with steroid/anti-infective combination drugs which can be attributed to the steroid component, the anti-infective component, or the combination. Exact incidence figures are not available since no denominator of treated patients is available.

Reactions occurring most often from the presence of the anti-infective ingredient are allergic sensitizations. The reactions due to the steroid component are: elevation of intraocular pressure (IOP) with possible development of glaucoma, and infrequent optic nerve damage; posterior subcapsular cataract formation; and delayed wound healing.

Secondary Infection: The development of secondary infection has occurred after use of combinations containing steroids and antimicrobials. Fungal infections of the cornea are particularly prone to develop coincidentally with long-term applications of steroid. The possibility of fungal invasion must be considered in any persistent corneal ulceration where steroid treatment has been used.

Secondary bacterial ocular infection following suppression of host responses also occurs.

DOSAGE AND ADMINISTRATION

Apply a small amount into the conjunctival sac(s) up to three or four times daily.

How to Apply Neomycin and Polymyxin B Sulfates and Dexamethasone Ophthalmic Ointment:

1. Tilt your head back.

2. Place a finger on your cheek just under your eye and gently pull down until a "V" pocket is formed between your eyeball and your lower lid.

3. Place a small amount (about 1/2 inch) of Neomycin and Polymyxin B Sulfates and Dexamethasone Ophthalmic Ointment in the "V" pocket. Do not let the tip of the tube touch your eye.

4. Look downward before closing your eye.

Not more than 8 g should be prescribed initially and the prescription should not be refilled without further evaluation as outlined in PRECAUTIONS above.

HOW SUPPLIED

3.5 g STERILE Ointment supplied in an aluminum tube with a white polyethylene tip and white polyethylene cap.

(NDC 71205-330-35).

STORAGE:

Store at 2°- 25°C (36°- 77°F).

Rx Only

Revised: October 2003

Distributed by :

FALCON Pharmaceuticals, Ltd.

Fort Worth, Texas 76134 USA

Manufactured by:

S.A. ALCON-COUVREUR N.V.

Puurs, Belgium

Relabeled by:

Proficient Rx LP

Thousand Oaks, CA 91320

0501

45057-A

PRINCIPAL DISPLAY PANEL

NDC 71205-330-35

Rx Only

Neomycin and Polymyxin B

Sulfates and

Dexamethasone

Ophthalmic Ointment

3.5 g STERILE